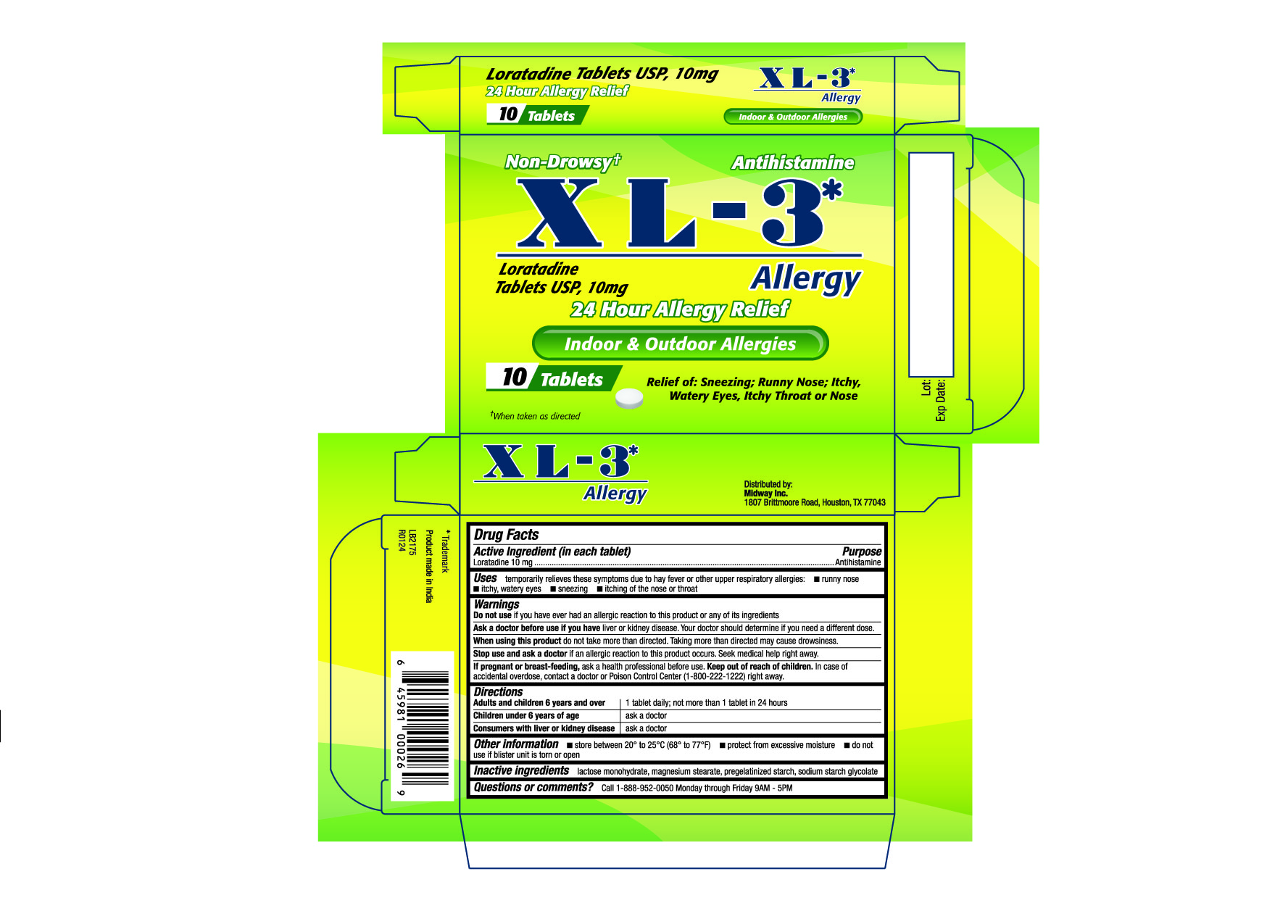 DRUG LABEL: XL - 3 Allergy
NDC: 63654-415 | Form: TABLET
Manufacturer: Selder, S.A. de C.V.
Category: otc | Type: HUMAN OTC DRUG LABEL
Date: 20240410

ACTIVE INGREDIENTS: LORATADINE 10 mg/1 1
INACTIVE INGREDIENTS: LACTOSE MONOHYDRATE; MAGNESIUM STEARATE; STARCH, CORN; SODIUM STARCH GLYCOLATE TYPE A

414 - XL-3 Allergy

Active ingredient(s)

Loratadine 10mg

Purpose

Antihistamine

Use(s)

temporarily relieves these symptoms due to hay fever or other upper respiratory allergies:

- runny nose
- itchy, watery eyes
- sneezing
- itching of the nose or throat

Warnings

Do not use

if you have ever had an allergic reaction to this product or any of its ingredients

Ask a doctor before use if

you have liver or kidney disease. Your doctor should determine if you need a different dose.

When using this product

do not take more than directed. Taking more than directed may cause drowsiness.

Stop use and ask a doctor if

if an allergic reaction to this product occurs. Seek medical help right away.

If pregnant or breastfeeding,

ask a health professional before use.

Keep out of reach of children

In case of accidental overdose, contact a doctor or Poison Control Center (1-800-222-1222) right away.

Directions

Adults and children 6 years and over: 1 tablet daily; not more than 1 tablet in 24 hours

Children under 6 years of age: ask a doctor

Consumers with liver or kidney disease: ask a doctor

Other information

- store between 20° to 25°C (68° to 77°F)
- protect from excessive moisture
- do not use if blister unit is torn or open

Inactive ingredients

lactose monohydrate, magnesium stearate, pregelatinized starch, sodium starch glycolate

Questions/Comments

Call 1-888-952-0050 Monday through Friday 9AM - 5PM

Principal Display Panel

XL - 3 Allergy